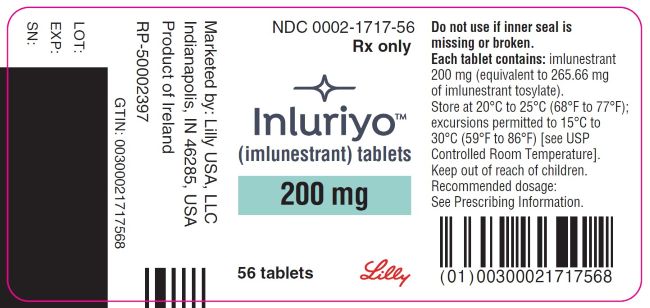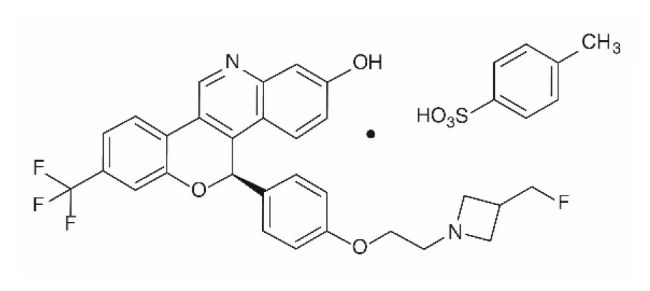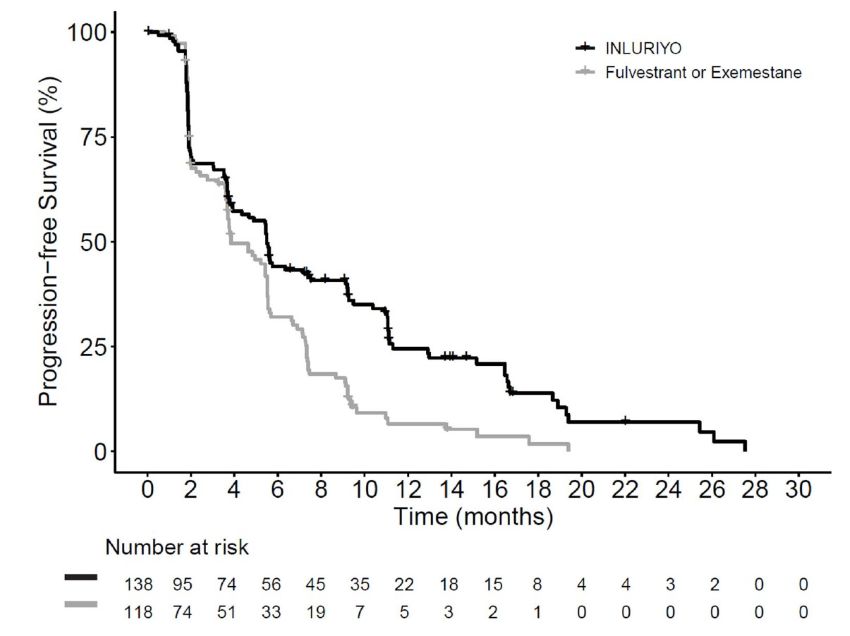 DRUG LABEL: Inluriyo
NDC: 0002-1717 | Form: TABLET, FILM COATED
Manufacturer: Eli Lilly and Company
Category: prescription | Type: HUMAN PRESCRIPTION DRUG LABEL
Date: 20251120

ACTIVE INGREDIENTS: imlunestrant 200 mg/1 1
INACTIVE INGREDIENTS: Croscarmellose Sodium; Hydroxypropyl Cellulose, Unspecified; Magnesium Stearate; Microcrystalline Cellulose; Polyethylene Glycol 3350; Polyvinyl Alcohol, Unspecified; Talc; Titanium Dioxide

HIGHLIGHTS OF PRESCRIBING INFORMATION

These highlights do not include all the information needed to use INLURIYO safely and effectively. See full prescribing information for INLURIYO.
INLURIYO (imlunestrant) tablets, for oral use
Initial U.S. Approval: 2025

1 INDICATIONS AND USAGE

INLURIYOTM is an estrogen receptor antagonist indicated for:

- treatment of adults with ER-positive, HER2-negative, ESR1-mutated advanced or metastatic breast cancer with disease progression following at least one line of endocrine therapy (1)

2 DOSAGE AND ADMINISTRATION

- Select patients for treatment based on the presence of ESR1 mutations. (2.1)
- The recommended dosage is 400 mg orally once daily, on an empty stomach. (2.2)
- Reduce the dose in patients with moderate or severe hepatic impairment (2.4, 8.6)
- Dosage modifications may be required. (2.3, 2.4, 2.5)

3 DOSAGE FORMS AND STRENGTHS

Tablets: 200 mg of imlunestrant. (3)

4 CONTRAINDICATIONS

- None. (4)

5 WARNINGS AND PRECAUTIONS

- Embryo-Fetal Toxicity: INLURIYO can cause fetal harm. Advise of the potential risk to a fetus and to use effective contraception. (5.1, 8.1, 8.3)

6 ADVERSE REACTIONS

The most common (incidence ≥10%) adverse reactions, including laboratory abnormalities were: hemoglobin decreased, musculoskeletal pain, calcium decreased, neutrophils decreased, AST increased, fatigue, diarrhea, ALT increased, triglycerides increased, nausea, platelets decreased, constipation, cholesterol increased, and abdominal pain. (6.1)

To report SUSPECTED ADVERSE REACTIONS, contact Eli Lilly and Company at 1-800-LillyRx (1-800-545-5979) or FDA at 1-800-FDA-1088 or www.fda.gov/medwatch.

7 DRUG INTERACTIONS

- Strong CYP3A Inhibitors: Avoid concomitant use with INLURIYO. If concomitant use cannot be avoided, decrease the INLURIYO dosage. (2.5, 7.1)
- Strong CYP3A Inducers: Avoid concomitant use with INLURIYO. If concomitant use cannot be avoided, increase the INLURIYO dosage (2.5, 7.1).

8 USE IN SPECIFIC POPULATIONS

- Lactation: Advise not to breastfeed. (8.2)

FULL PRESCRIBING INFORMATION

1 INDICATIONS AND USAGE

INLURIYO is indicated for the treatment of adults with estrogen receptor (ER)-positive, human epidermal growth factor receptor 2 (HER2)-negative, estrogen receptor-1 (ESR1)-mutated advanced or metastatic breast cancer with disease progression following at least one line of endocrine therapy.

2 DOSAGE AND ADMINISTRATION

2.1 Patient Selection

Select patients for treatment of ER-positive, HER2-negative advanced or metastatic breast cancer with INLURIYO based on the presence of ESR1 mutation(s) in a plasma specimen using an FDA-approved test [see Indications and Usage (1) and Clinical Studies (14.1)].

Information on FDA-approved tests for the detection of ESR1 mutations in breast cancer is available at: https://www.fda.gov/CompanionDiagnostics.

2.2 Recommended Dosage and Administration

The recommended dosage of INLURIYO is 400 mg orally once daily until disease progression or unacceptable toxicity.

Take on an empty stomach at least 2 hours before food, or 1 hour after food [see Clinical Pharmacology (12.3)]. Take INLURIYO tablets at approximately the same time daily. Swallow the tablets whole. Do not split, crush, or chew the tablets.

Pre/perimenopausal women and men should receive a gonadotropin-releasing hormone agonist (GnRH) according to current clinical practice standards.

If patient misses a dose by 6 or more hours or vomits, instruct the patient to take the next dose the following day at its scheduled time.

2.3 Dosage Modifications for Adverse Reactions

The recommended INLURIYO dosage modifications for adverse reactions are provided in Tables 1 and 2.

The recommended dose reduction is to 200 mg once daily.

Permanently discontinue INLURIYO in patients who are unable to tolerate 200 mg once daily.

Table 1: INLURIYO Dosage Modification - Adverse Reactions (except hepatotoxicity)
Grade | INLURIYO Dosage Modifications
Persistent or recurrent Grade 2 that does not resolve with maximal supportive measures within 7 days to baseline or Grade 1 | Suspend until toxicity resolves to baseline or ≤Grade 1. Resume INLURIYO at the same dose level.
Grade 3 or 4 (except non-hepatic asymptomatic laboratory changes) | Suspend until toxicity resolves to baseline or ≤Grade 1. Resume INLURIYO at next lower dose level.

Table 2: INLURIYO Dosage Modification - Hepatotoxicity
Monitor alanine aminotransferase (ALT)/aspartate aminotransferase (AST) during imlunestrant therapy as clinically indicated.
Liver Transaminase | INLURIYO Dosage Modifications
Persistent or Recurrent: AST/ALT >3.0-5.0×ULN | Suspend until toxicity resolves to baseline or to >ULN-3.0×ULN. Resume INLURIYO at the same dose level.
If AST/ALT at baseline is within the normal range: AST/ALT >5.0-20×ULN Or If AST/ALT at baseline is above ULN: AST/ALT ≥3 × baseline (if AST/ALT≥1.5 x ULN at baseline) Or AST/ALT >8 × ULN (whichever is the lower threshold) | Suspend until toxicity resolves to baseline or to >ULN-3.0×ULN. Resume INLURIYO at next lower dose level or discontinue if receiving 200 mg daily.
AST/ALT >20.0×ULN Or ALT or AST ≥ 3 × ULN concurrent with TBL ≥ 2 × ULN (if ALT or AST < 1.5 × ULN at baseline), in the absence of cholestasis Or ALT or AST ≥ 2 × baseline concurrent with TBL ≥ 2 × ULN (if ALT or AST ≥ 1.5 × ULN at baseline), in the absence of cholestasis | Discontinue INLURIYO.
Abbreviation: ALT = alanine aminotransferase, AST = aspartate aminotransferase, TBL=total bilirubin, ULN = upper limit of normal.

2.4 Dosage in Patients with Hepatic Impairment

The recommended dosage of INLURIYO for patients with moderate (Child-Pugh B) or severe (Child-Pugh C) hepatic impairment is 200 mg once daily. Monitor for increased adverse reactions [see Clinical Pharmacology (12.3)].

2.5 Dosage Modifications for Drug Interactions

Strong CYP3A Inhibitors

Avoid concomitant use with strong CYP3A inhibitors. If concomitant use cannot be avoided, decrease the INLURIYO dosage to 200 mg once daily [see Drug Interactions (7.1)].

Strong CYP3A Inducers

Avoid concomitant use with strong CYP3A inducers. If concomitant use cannot be avoided, increase the INLURIYO dosage to 600 mg once daily [see Drug Interactions (7.1)].

3 DOSAGE FORMS AND STRENGTHS

INLURIYO tablets contain 200 mg imlunestrant and are white, film coated-capsule-shaped tablets, with “LILLY” on one side and “1717” and elongated 4-point starburst on the other side.

4 CONTRAINDICATIONS

None.

5 WARNINGS AND PRECAUTIONS

5.1 Embryo-Fetal Toxicity

Based on findings in animals and its mechanism of action, INLURIYO can cause fetal harm when administered to a pregnant woman. In an animal reproduction study, oral administration of imlunestrant to pregnant rats during the period of organogenesis led to embryo-fetal mortality and structural abnormalities at maternal exposures that were below the human exposure at the recommended dose based on AUC.

Advise pregnant women and females of reproductive potential of the potential risk to a fetus. Advise females of reproductive potential to use effective contraception during treatment with INLURIYO and for 1 week after the last dose. Advise male patients with female partners of reproductive potential to use effective contraception during treatment with INLURIYO and for 1 week after the last dose [see Use in Specific Populations (8.1, 8.3) and Clinical Pharmacology (12.1)].

6 ADVERSE REACTIONS

6.1 Clinical Trial Experience

Because clinical trials are conducted under widely varying conditions, adverse reaction rates observed in the clinical trials of a drug cannot be directly compared to rates in the clinical trials of another drug and may not reflect the rates observed in practice.

The safety of INLURIYO was evaluated in 651 patients with ER+, HER2- locally advanced or metastatic breast cancer previously treated with endocrine therapy with or without a prior CDK4/6 inhibitor in EMBER-3 [see Clinical Studies (14.1)]. Patients received INLURIYO 400 mg orally, once daily (n=327), or standard of care (n=324) consisting of either fulvestrant (n=292) or exemestane (n=32). Among patients who were treated with INLURIYO, the median duration of exposure was 5.6 months (range: 0.2 to 28.6 months) in EMBER-3.

Serious adverse reactions occurred in 10% of patients who received INLURIYO. Serious adverse reactions in > 1% of patients included pleural effusion (1.2%). Fatal adverse reactions occurred in 1.8% of patients who received INLURIYO, including cardiac arrest, acute myocardial infarction, right ventricular failure, hypovolemic shock, and upper gastrointestinal hemorrhage (each 0.3%).

Permanent treatment discontinuation of INLURIYO due to an adverse reaction occurred in 4.6% of patients. Adverse reactions which resulted in permanent discontinuation of INLURIYO included increased alanine aminotransferase (0.9%), abdominal pain, fatigue, fractured sacrum, hepatotoxicity, neuropathy peripheral, and pyrexia (each 0.3%).

Dosage interruption of INLURIYO due to an adverse reaction occurred in 10% of patients. Adverse reactions which required dosage interruption in >0.5% were vomiting (1.5%); increased aspartate aminotransferase and COVID-19 (each 0.9%); and increased alanine aminotransferase, anemia, diarrhea, decreased neutrophil count, and pyrexia (each 0.6%).

Dose reductions of INLURIYO due to an adverse reaction occurred in 2.4% of patients. Adverse reactions which required dose reductions were increased aspartate aminotransferase (0.6%); and increased alanine aminotransferase, anemia, fatigue, interstitial lung disease, nausea, neutropenia, and vomiting (each 0.3%).

The most common (≥10%) adverse reactions, including laboratory abnormalities, were hemoglobin decreased, musculoskeletal pain, calcium decreased, neutrophils decreased, AST increased, fatigue, diarrhea, ALT increased, triglycerides increased, nausea, platelets decreased, constipation, cholesterol increased, and abdominal pain.

Table 3 summarizes the adverse reactions in EMBER-3.

Table 3: Adverse Reactions (≥10%) in Patients Who Received INLURIYO in EMBER-3
Adverse Reactiona | INLURIYO N=327 |  | Fulvestrant or Exemestane N=324
Adverse Reactiona | All Grades % | Grades 3 or 4 % | All Grades % | Grades 3 or 4 %
Musculoskeletal Disorders
Musculoskeletal Pain | 30 | 3.7 | 29 | 1.9
General Disorders and Administration Site Conditions
Fatigueb | 23 | 0.3 | 14 | 0.6
Gastrointestinal Disorders
Diarrhea | 22 | 0.6 | 12 | 0.0
Nausea | 17 | 0.3 | 13 | 0.0
Constipation | 10 | 0 | 6 | 0.3
Abdominal painb | 10 | 0.3 | 6 | 0.6
a Adverse reactions were graded using NCI CTCAE version 5.0.
b Includes other related terms

Clinically relevant adverse reactions (<10%) in patients who received INLURIYO included: vomiting (9%), headache (9%), cough (9%), decreased appetite (8%), hot flush (7%), pruritus (3.7%), dyspepsia (2.8%), and stomatitis (2.4%).

Table 4 summarizes the laboratory abnormalities in EMBER-3.

Table 4: Select Laboratory Abnormalities (≥10%) That Worsened from Baseline in Patients Who Received INLURIYO in EMBER-3
Lab Abnormalitya | INLURIYOb |  | Fulvestrant or Exemestaneb
Lab Abnormalitya | All Grades % | Grades 3 or 4 % | All Grades % | Grades 3 or 4 %
Hematology
Hemoglobin decreased | 30 | 1.2 | 35 | 3.4
Neutrophils decreased | 26 | 4 | 29 | 4.7
Platelets decreased | 16 | 1.8 | 14 | 1.3
Chemistry
Calcium decreased | 26 | 0 | 19 | 0.6
Aspartate aminotransferase increased | 25 | 1.9 | 27 | 2.3
Alanine aminotransferase increased | 21 | 1.3 | 23 | 1.0
Triglycerides increased | 21 | 0 | 22 | 1.2
Cholesterol increased | 10 | 0 | 12 | 0
a Graded according to NCI CTCAE version 5
b The denominator used to calculate the rate varied from 252 to 325 based on the number of patients with a baseline value and at least one post-treatment value.

7 DRUG INTERACTIONS

7.1 Effects of Other Drugs on INLURIYO

Strong CYP3A Inhibitors

Avoid concomitant use of INLURIYO with strong CYP3A inhibitors. If concomitant use cannot be avoided, reduce the dosage of INLURIYO [see Dosage and Administration (2.5), Clinical Pharmacology (12.3)].

Imlunestrant is a CYP3A substrate. Concomitant use of a strong CYP3A inhibitor increases imlunestrant exposure [see Clinical Pharmacology (12.3)], which may increase the risk of INLURIYO-associated adverse reactions.

Strong CYP3A Inducers

Avoid concomitant use of INLURIYO with strong CYP3A inducers. If concomitant use cannot be avoided, increase the dosage of INLURIYO [see Dosage and Administration (2.5), Clinical Pharmacology (12.3)].

Imlunestrant is a CYP3A substrate. Concomitant use of a strong CYP3A inducer decreases imlunestrant exposure [see Clinical Pharmacology (12.3)], which may reduce effectiveness of INLURIYO.

7.2 Effects of INLURIYO on Other Drugs

P-gp or BCRP Substrates

Avoid concomitant use unless otherwise recommended in the Prescribing Information for P-gp or BCRP substrates where minimal concentration changes may lead to serious adverse reactions.

Imlunestrant inhibits both P-gp and BCRP. Imlunestrant increases exposure of P-gp and BCRP substrates, which may increase the risk of adverse reactions related to these substrates [see Clinical Pharmacology (12.3)].

8 USE IN SPECIFIC POPULATIONS

8.1 Pregnancy

Risk Summary

Based on findings in animals and its mechanism of action, INLURIYO can cause fetal harm when administered to a pregnant woman [see Clinical Pharmacology (12.1)]. There are no available human data on INLURIYO use in pregnant women to inform the drug-associated risk. In an animal reproduction study, oral administration of imlunestrant to pregnant rats during the period of organogenesis led to embryo-fetal mortality and structural abnormalities at maternal exposures below the human exposure at the recommended dose based on AUC (see Data). Advise pregnant women and females of reproductive potential of the potential risk to a fetus.

The background risk of major birth defects and miscarriage for the indicated population is unknown. However, the background risk in the U.S. general population of major birth defects is 2 to 4% and of miscarriage is 15 to 20% of clinically recognized pregnancies.

Data

Animal Data

In an embryo-fetal development study, imlunestrant was administered orally to pregnant rats during the period of organogenesis from gestation day 6 to 17 at doses of 0.3, 3, and 30 mg/kg/day. Imlunestrant caused embryo-fetal mortality (increased resorption, reduced number of live fetuses) at ≥0.3 mg/kg/day, approximately 0.1 times the human AUC at the recommended dose. Early delivery, fetal malformations (including small jaw, protruding tongue, malrotated, and hyperextended hindlimb) and fetal variations (edema localized subcutis) were observed at ≥3 mg/kg/day, approximately 1 time the human AUC at the recommended dose.

8.2 Lactation

Risk Summary

There are no data on the presence of imlunestrant or its metabolites in human milk, its effects on the breastfed child, or on milk production. Because of the potential for serious adverse reactions in the breastfed child, advise lactating women to not breastfeed during treatment with INLURIYO and for 1 week after the last dose.

8.3 Females and Males of Reproductive Potential

INLURIYO can cause fetal harm when administered to a pregnant woman [see Use in Specific Populations (8.1)].

Pregnancy Testing

Verify the pregnancy status in females of reproductive potential prior to initiating INLURIYO.

Contraception

Females

Advise females of reproductive potential to use effective contraception during treatment with INLURIYO and for 1 week after the last dose.

Males

Advise male patients with female partners of reproductive potential to use effective contraception during treatment with INLURIYO and for 1 week after the last dose.

Infertility

Based on findings in animals, INLURIYO may impair fertility in females and males of reproductive potential. Findings in animals were reversible [see Nonclinical Toxicology (13.1)].

8.4 Pediatric Use

The safety and effectiveness of INLURIYO have not been established in pediatric patients.

8.5 Geriatric Use

Of 327 patients who received INLURIYO in the EMBER-3 study, 118 patients were ≥ 65 years of age and 37 patients were ≥ 75 years of age. No overall differences in safety or effectiveness of INLURIYO have been observed between patients 65 years of age and older and younger adult patients.

8.6 Hepatic Impairment

Reduce the dose of INLURIYO in patients with moderate (Child-Pugh B) or severe (Child-Pugh C) hepatic impairment. No dosage modification is recommended for patients with mild hepatic impairment (Child-Pugh A) [see Dosage and Administration (2.4) and Clinical Pharmacology (12.3)].

11 DESCRIPTION

INLURIYO tablets contain imlunestrant, an estrogen receptor antagonist. The chemical name for imlunestrant tosylate is (5R)-5-(4-(2-(3-(flouromethyl)azetidin-1-yl)ethoxy)phenyl)-8-(trifluoromethyl)-5H-(1)benzopyrano(4,3-c)quinolin-2-ol, tosylate salt (1:1). Imlunestrant tosylate is a white to practically white to yellow powder with the empirical formula C29H24F4N2O3.C7H8O3S and a molecular weight 696.71 g/mol. The aqueous solubility of imlunestrant tosylate is slightly soluble at low pH, insoluble at neutral pH, and sparingly soluble at high pH. The chemical structure of imlunestrant tosylate is shown below:

INLURIYO are tablets for oral administration. Each INLURIYO tablet is available as capsule-shaped, film-coated tablet that contains 200 mg imlunestrant (equivalent to 265.66 mg imlunestrant tosylate). The tablet contains the following inactive ingredients: croscarmellose sodium, hydroxypropyl cellulose, magnesium stearate, and microcrystalline cellulose. The tablets are coated using a common white coating, which consists of polyethylene glycol, polyvinyl alcohol, talc, and titanium dioxide.

12 CLINICAL PHARMACOLOGY

12.1 Mechanism of Action

Imlunestrant is an estrogen receptor (ER) antagonist that binds to ERα. In vitro, imlunestrant induced degradation of ERα, leading to inhibition of ER-dependent gene transcription and cellular proliferation in ER+ breast cancer cells. Imlunestrant demonstrated in vitro and in vivo anti-tumor activity in ER+ breast cancer xenograft models, including models with ESR1 mutations.

12.2 Pharmacodynamics

Imlunestrant exposure-response relationships and the time course of pharmacodynamics have not been fully characterized.

Cardiac Electrophysiology

At 2 times the mean maximum concentration observed with the approved recommended dose, a mean increase in the QTc interval >20 msec was not observed.

12.3 Pharmacokinetics

Imlunestrant pharmacokinetics were observed at steady state at the approved recommended dosage and are presented as mean (%CV) unless otherwise specified. The maximum concentration (Cmax) of imlunestrant is 141 ng/mL (45%) and the area under the concentration-time curve (AUC) is 2,400 ng*h/mL (46%). Imlunestrant Cmax and AUC increase in a dose proportional manner over a dosage range of 200 mg to 1,200 mg (0.5 to 3 times the approved recommended dosage) once daily. Steady-state is reached in approximately 6 days and the accumulation is 2.3-fold based on AUC.

Absorption

Imlunestrant absolute oral bioavailability after a single oral 400 mg dose is 10% (32%). Imlunestrant median (min, max) time to maximum plasma concentration (Tmax) is 4 (2, 8) hours.

Effect of Food

Imlunestrant AUC increased 2-fold and Cmax increased 3.6-fold following administration with a low-fat meal (approximately 475 calories with 13% fat, 16% protein, and 71% carbohydrates). The effect of high-fat meal (approximately 800-1,000 calories with 500-600 calories from fat) on imlunestrant exposures is unknown.

Distribution

The apparent (oral) volume of distribution is 8,120 L (69%). Imlunestrant protein binding is >99% and is not concentration dependent.

Elimination

Imlunestrant elimination half-life is 30 hours with an estimated apparent clearance of 166 L/h (51%).

Metabolism

Imlunestrant is metabolized by sulfation, CYP3A4, and direct glucuronidation (UGT1A1, 1A3, 1A8, 1A9, 1A10).

Excretion

After a single dose of radiolabeled imlunestrant 400 mg to healthy subjects, 97% of the dose was recovered in feces (62% unchanged) and 0.3% in urine.

Specific Populations

No clinically significant differences in the pharmacokinetics of imlunestrant based on age (28 to 95 years), race (64% White, 23% Asian, and 5% Black or African American), ethnicity (74% non-Hispanic/Latino, 17% Hispanic/Latino), body weight (36 to 145 kg), mild to moderate (eGFR 30 to 89 mL/min, estimated by CKD-EPI equation) renal impairment, or UGT1A1 genetic polymorphisms (e.g., UGT1A1*1/*28 or UGT1A1*28/*28). The effect of severe (eGFR 15 to 29 mL/min) renal impairment and renal impairment requiring dialysis on imlunestrant pharmacokinetics is unknown.

Patients with Hepatic Impairment

Imlunestrant AUC increased 2.2-fold in subjects with moderate hepatic impairment (Child-Pugh B) and 3.1-fold in subjects with severe hepatic impairment (Child-Pugh C). No clinically significant differences in the pharmacokinetics of imlunestrant were observed in subjects with mild hepatic impairment (Child-Pugh A).

Drug Interaction Studies

Clinical Studies

Strong CYP3A Inhibitors: Imlunestrant AUC increased 2.1-fold and Cmax increased 1.9-fold following concomitant use of itraconazole (strong CYP3A inhibitor) for multiple days.

Strong CYP3A Inducers: Imlunestrant AUC decreased by 42% and Cmax decreased by 29% following concomitant use of carbamazepine (strong CYP3A inducer) for multiple days.

P-gp Substrates: Digoxin (P-gp substrate) AUC increased 1.4-fold and Cmax increased 1.6-fold following concomitant use of imlunestrant.

BCRP Substrates: Rosuvastatin (BCRP substrate) AUC increased 1.5-fold and Cmax increased 1.6-fold following concomitant use with imlunestrant.

Other Drugs: No clinically significant differences in the pharmacokinetics of imlunestrant were observed when used concomitantly with omeprazole (gastric acid-reducing agent) or quinidine (P-gp inhibitor).

No clinically significant differences in the pharmacokinetics of midazolam (CYP3A substrate), repaglinide (CYP2C8 substrate), omeprazole (CYP2C19 substrate), or dextromethorphan (CYP2D6 substrate) were observed when used concomitantly with imlunestrant.

In Vitro Studies

CYP Enzymes: Imlunestrant is an inhibitor of CYP2B6 and CYP2C9 but is not an inhibitor of CYP1A2. Imlunestrant is not an inducer of CYP1A2, CYP2B6, or CYP2C9.

Transporter Systems: Imlunestrant is not a substrate of BCRP, OCT1, OATP1B1, or OATP1B3.

13 NONCLINICAL TOXICOLOGY

13.1 Carcinogenesis, Mutagenesis, Impairment of Fertility

Carcinogenesis

Carcinogenicity studies have not been conducted with imlunestrant.

Mutagenesis

Imlunestrant was not mutagenic in the bacterial reverse mutation (Ames) assay. Imlunestrant was clastogenic in an in vitro human lymphocyte micronucleus assay. Imlunestrant was not genotoxic in an in vivo rat bone marrow micronucleus test and did not induce DNA breaks in the liver and duodenum comet assays.

Impairment of Fertility

Fertility studies with imlunestrant in animals have not been conducted. In repeat-dose toxicity studies up to 6 months in rats and 3 months in cynomolgus monkeys, oral administration of imlunestrant resulted in follicular cysts in the ovary and atrophy in the vagina, cervix, and uterus at doses ≥ 10 mg/kg/day in rats (≥ 4 times the human AUC at the recommended dose) and ≥ 15 mg/kg/day in cynomolgus monkeys (≥1 times the human AUC at the recommended dose). Decreased sperm and cellular debris in the epididymis and spermatid retention in the testis were observed in male rats at ≥10 mg/kg/day. The effects of imlunestrant on male and female reproductive organs were reversible in rats following a 3-month recovery period. Reversibility was not assessed in cynomolgus monkeys.

13.2 Animal Toxicology and/or Pharmacology

In a 6-month repeat-dose toxicity study, oral administration of imlunestrant to rats resulted in epithelial hyperplasia in the urinary bladder, granulosa cell hyperplasia in the ovary, and hyperplasia in the mammary gland at doses ≥ 10 mg/kg/day (≥ 4 times the human AUC at the recommended dose). These effects, except urinary bladder effects, were reversible after a 3-month recovery period.

14 CLINICAL STUDIES

The efficacy of INLURIYO was evaluated in EMBER-3 (NCT04975308), a randomized, open-label, active-controlled, multicenter trial that enrolled 874 adult patients with ER+, HER2- locally advanced or metastatic breast cancer, who were previously treated with an aromatase inhibitor either alone or in combination with a CDK4/6 inhibitor. Patients were excluded if they were eligible to receive a PARP inhibitor. Patients were required to have progressed:

- Within 12 months of completing neoadjuvant or adjuvant aromatase inhibitor therapy with no systemic treatment for recurrent disease or
- Greater than 12 months after neoadjuvant or adjuvant endocrine therapy or de novo metastatic disease and had progressed on only one line of aromatase inhibitor therapy.

Patients were randomized 1:1:1 to INLURIYO 400 mg orally once daily; or investigator's choice of endocrine therapy [fulvestrant 500 mg IM on days 1, 15, 29, and once monthly thereafter (n=111) or exemestane 25 mg orally once daily (n=6)]; or an additional investigational combination regimen. Randomization was stratified by previous treatment with CDK4/6 inhibitor (yes vs no), presence of visceral metastasis (yes vs no), and region (East Asia vs North America/Western Europe vs Others). ESR1m status was determined by blood circulating tumor deoxyribonucleic acid (ctDNA) analysis using the Guardant360 CDx assay and was limited to specific ESR1 mutations in the ligand binding domain. Patients were treated until disease progression or unacceptable toxicity.

The major efficacy outcome was investigator assessed progression-free survival (PFS) according to RECIST v1.1. Other efficacy measures included overall survival (OS), blinded independent review committee (BIRC)-assessed PFS, and objective response rate (ORR).

Among the patients on the INLURIYO arm or investigator's choice of endocrine therapy who were positive for ESR1m (N=256), the median age was 61 years (range: 28-85 years); all patients were female, of which 11% were pre/perimenopausal; 61% were White, 26% Asian, 4% Black, 4% were American Indian or Alaskan Native, 4.7% missing, 0.8% multiple, 19% were Hispanic/Latino; and baseline ECOG performance status was 0 (63%) or 1 (37%). Most patients had visceral metastasis (59%) at baseline. Of the patients enrolled, 21% had received no endocrine therapy and 79% had received one line of endocrine therapy in the advanced or metastatic setting. Overall, 70% of patients were treated with a prior CDK4/6i, 2.3% treated in the adjuvant setting and 67% treated in the advanced or metastatic setting.

The efficacy results from these patients are summarized in Table 5 and Figure 1. There was a statistically significant difference in investigator-assessed PFS in the ESR1m population for INLURIYO compared to investigator's choice of endocrine therapy (fulvestrant or exemestane). PFS assessment based on a BIRC was consistent with the investigator assessment. At the time of PFS analysis, overall survival data was immature with 31% of deaths in the ESR1m population.

Table 5: Efficacy Results for Patients with ESR1m in EMBER-3
 | INLURIYO N=138 | Fulvestrant or Exemestane N=118
Progression-free Survival (PFS) a, b
Number of PFS Events, n (%) | 109 (79) | 102 (86)
Median in months (95% CI) | 5.5 (3.9, 7.4) | 3.8 (3.7, 5.5)
Hazard Ratio (95% CI)c | 0.62 (0.46, 0.82)
p-valued | 0.0008
Objective Response Rateb
Patients with Measurable Disease | 112 | 91
ORR (95% CI) | 14.3 (7.8, 20.8) | 7.7 (2.2, 13.2)
Complete response rate, % | 0.9 | 0
Partial response rate, % | 13.4 | 7.7
a Investigator Assessed
b per RECIST v1.1
c Based on the stratified Cox proportional hazard model
d Two-sided p-value based on stratified log-rank test (compared to a significance level of 0.04)

Figure 1: Kaplan-Meier Plot of Investigator-Assessed PFS for Patients with ESR1 m, Treated with INLURIYO or Fulvestrant/Exemestane in EMBER-3

16 HOW SUPPLIED/STORAGE AND HANDLING

How Supplied

INLURIYO 200 mg tablets are white capsule-shaped tablets with “LILLY” on one side and “1717” and an elongated 4-point starburst on the other side.

INLURIYO 200 mg tablets are supplied in either a 28-count or 56-count bottle configuration.

- 28-count: NDC 0002-1717-28
- 56-count: NDC 0002-1717-56

Storage and Handling

Store at 20°C to 25°C (68°F to 77°F). Excursions between 15°C to 30°C (59°F to 86°F) are permitted [see USP Controlled Room Temperature].

Disposal

Dispose unused medication via a take-back option if available. Otherwise, follow FDA instructions for disposing medication in the household trash, www.fda.gov/drugdisposal. Do NOT flush down the toilet.

17 PATIENT COUNSELING INFORMATION

Advise patients to read the FDA-approved patient labeling (Patient Information).

Dyslipidemia

Advise patients that hypercholesterolemia and hypertriglyceridemia may occur while taking INLURIYO. Inform patients that lipid profile monitoring will be performed prior to starting and periodically while taking INLURIYO [see Adverse Reactions (6.1)].

Embryo-Fetal Toxicity

Advise pregnant women and females of reproductive potential of the potential risk to a fetus. Advise females to inform their healthcare provider of a known or suspected pregnancy [see Warnings and Precautions (5.1) and Use in Specific Populations (8.1)].

Advise females of reproductive potential to use effective contraception during treatment with INLURIYO and for 1 week after the last dose. Advise male patients with female partners of reproductive potential to use effective contraception during treatment with INLURIYO and for 1 week after the last dose [see Use in Specific Populations (8.3)].

Lactation

Advise women not to breastfeed during treatment with INLURIYO and for 1 week after the last dose [see Use in Specific Populations (8.2)].

Infertility

Advise males and females of reproductive potential that INLURIYO may impair fertility [see Use in Specific Populations (8.3)].

Drug Interactions

Advise patients to inform their healthcare providers of all concomitant medications, including prescription medicines, over the counter drugs, and herbal products [see Drug Interactions (7.1, 7.2)].

Dosing Instructions

Instruct patients to take INLURIYO at approximately the same time each day and to swallow the tablet(s) whole. Tablets should not be chewed, crushed, or split prior to swallowing [see Dosage and Administration (2.1)].

Advise patients to take INLURIYO without food, either 2 hours before food or 1 hour after food [see Dosage and Administration (2.1)].

Instruct patient that if a dose of INLURIYO is missed by more than 6 hours or vomiting occurs, skip the dose and take the next dose the following day at its regularly scheduled time [see Dosage and Administration (2.1)].

Marketed by: Lilly USA, LLC, Indianapolis, IN 46285, USA

Copyright © 2025, Eli Lilly and Company. All rights reserved.

INL-0001-USPI-202509

PATIENT INFORMATION
INLURIYOTM (en-loo-ree-yoh)
imlunestrant
tablets

What is INLURIYO?
INLURIYO is a prescription medicine used to treat adults with estrogen receptor (ER)-positive, human epidermal growth factor receptor 2 (HER2)-negative, estrogen receptor-1 (ESR1)-mutated advanced breast cancer or breast cancer that has spread to other parts of the body (metastatic), and whose disease has progressed after at least 1 line of endocrine therapy.
Your healthcare provider will perform a test to make sure that INLURIYO is right for you.
It is not known if INLURIYO is safe and effective in children.

Before taking INLURIYO, tell your healthcare provider about all of your medical conditions including if you:

- have liver problems.
- are pregnant or plan to become pregnant. INLURIYO can harm your unborn baby.

Females who are able to become pregnant:

- Your healthcare provider will do a pregnancy test before you start treatment with INLURIYO.
- Use effective birth control (contraception) during treatment with INLURIYO and for 1 week after the last dose.
- Tell your healthcare provider right away if you become pregnant or think you may be pregnant during treatment with INLURIYO.

Males with female partners who are able to become pregnant:

- Use effective birth control (contraception) during treatment with INLURIYO and for 1 week after the last dose.

- are breastfeeding or plan to breastfeed. It is not known if INLUIRYO passes into breastmilk. Do not breastfeed during treatment with INLURIYO and for 1 week after the last dose.

Tell your healthcare provider about all of the medicines you take, including prescription and over-the counter medicines, vitamins, and herbal supplements. INLURIYO and other medicines may affect each other causing side effects. Know the medicines you take. Keep a list of them to show your healthcare provider or pharmacist when you get a new medicine.

How should I take INLURIYO?

- Take INLURIYO exactly as your healthcare provider tells you.
- Do not stop taking INLURIYO or change the dose unless your healthcare provider tells you to.
- Take INLURIYO 1 time a day at about the same time each day.
- Take INLURIYO on an empty stomach, at least 2 hours before food or 1 hour after food.
- Swallow INLURIYO tablets whole. Do not chew, crush, or split the tablets.
- If you miss a dose of INLURIYO by 6 or more hours or vomit after taking INLURIYO, do not take another dose on that day. Take your next dose the following day at your regularly scheduled time.

What are the possible side effects of INLURIYO?
The most common side effects of INLURIYO include:

- decreased hemoglobin (anemia)
- muscle and joint pain
- decreased white blood cell counts
- increased liver function tests
- decreased calcium blood levels
- tiredness
- diarrhea
- increased triglyceride and cholesterol blood levels. Your healthcare provider will check your blood levels before and during treatment with INLURIYO.

- nausea
- decreased platelet counts
- constipation
- stomach-area (abdominal) pain

Your healthcare provider may change your dose, temporarily stop, or completely stop treatment with INLURIYO if you develop certain side effects.
INLURIYO may affect fertility in males and in females who are able to become pregnant. Talk to your healthcare provider if this is a concern for you.
These are not all of the possible side effects of INLURIYO.
Call your doctor for medical advice about side effects. You may report side effects to FDA at 1-800-FDA-1088.

How should I store INLURIYO?

- Store INLURIYO at room temperature between 68°F to 77°F (20°C to 25°C).
- Throw away (dispose of) unused INLURIYO by a medicine take-back program if available. If no take-back program is available, visit www.fda.gov/drugdisposal for instructions on how to throw away medicines in the household trash.
- Do not flush INLURIYO down the toilet.

Keep INLURIYO and all medicines out of the reach of children.

General information about the safe and effective use of INLURIYO.
Medicines are sometimes prescribed for purposes other than those listed in a Patient Information leaflet. Do not use INLURIYO for a condition for which it was not prescribed. Do not give INLURIYO to other people, even if they have the same symptoms you have. It may harm them. You can ask your pharmacist or healthcare provider for more information about INLURIYO.

What are the ingredients in INLURIYO?
Active ingredient: imlunestrant
Inactive ingredients: croscarmellose sodium, hydroxypropyl cellulose, magnesium stearate, and microcrystalline cellulose. The tablet coating contains polyethylene glycol, polyvinyl alcohol, talc, and titanium dioxide.
INLURIYO is a trademark of Eli Lilly and Company. All rights reserved.
Marketed by: Lilly USA, LLC, Indianapolis, IN 46285, USA
Copyright © 2025, Eli Lilly and Company. All rights reserved.
For more information, go to www.INLURIYO.com or call 1-800-545-5979

This Patient Information has been approved by the U.S. Food and Drug Administration

Issued: September 2025

INL-0001-PPI-202509

PACKAGE LABEL – Inluriyo 200 mg 56 count bottle

NDC 0002-1717-56

Rx only

InluriyoTM

(imlunestrant) tablets

200 mg

56 tablets

Lilly